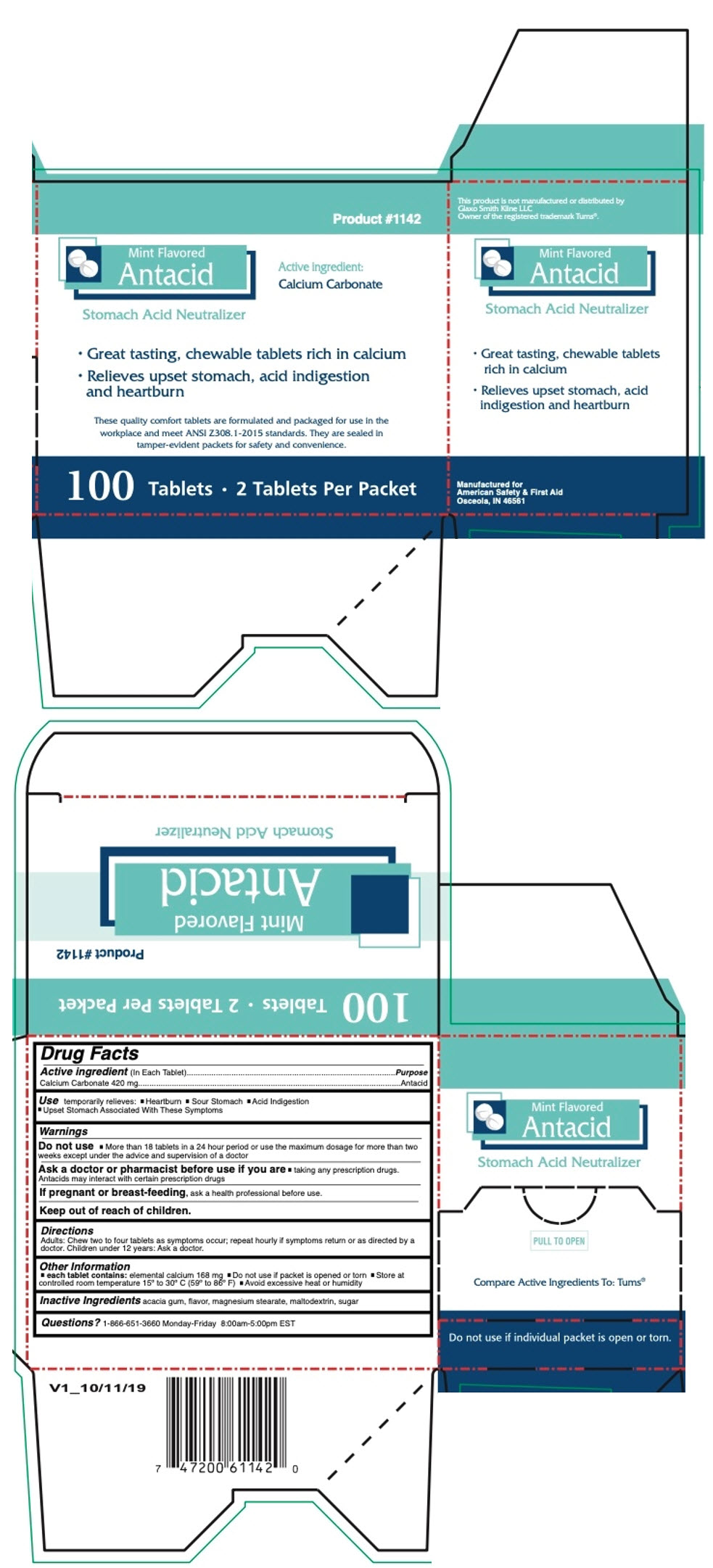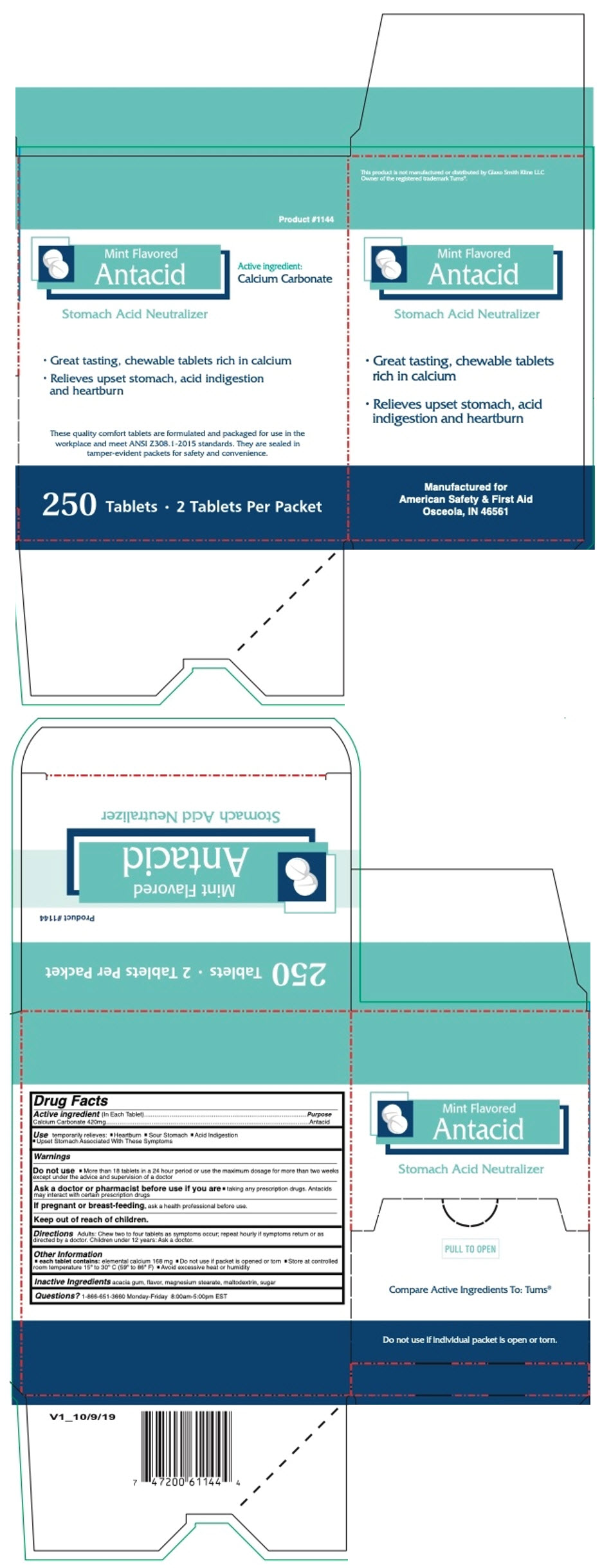 DRUG LABEL: MINT ANTACID 100
NDC: 73598-1142 | Form: TABLET, CHEWABLE
Manufacturer: JHK Inc dba American Safety & First Aid
Category: otc | Type: HUMAN OTC DRUG LABEL
Date: 20240424

ACTIVE INGREDIENTS: CALCIUM CARBONATE 420 mg/1 1
INACTIVE INGREDIENTS: ACACIA; MAGNESIUM STEARATE; MALTODEXTRIN; SUCROSE

MINT ANTACID

Drug Facts

Active ingredient (In Each Tablet)

Calcium Carbonate 420mg

Purpose

Antacid

Use

temporarily relieves:

- Heartburn
- Sour Stomach
- Acid Indigestion
- Upset Stomach Associated With These Symptoms

Warnings

Do not use

- More than 18 tablets in a 24 hour period or use the maximum dosage for more than two weeks except under the advice and supervision of a doctor

Ask a doctor or pharmacist before use if you are

- taking any prescription drugs. Antacids may interact with certain prescription drugs

PREGNANCY OR BREAST FEEDING

If pregnant or breast-feeding, ask a health professional before use.

Keep out of reach of children.

Directions

Adults: Chew two to four tablets as symptoms occur; repeat hourly if symptoms return or as directed by a doctor. Children under 12 years: Ask a doctor.

Other Information

- each tablet contains: elemental calcium 168 mg
- Do not use if packet is opened or torn
- Store at controlled room temperature 15º to 30º C (59º to 86º F)
- Avoid excessive heat or humidity

Inactive Ingredients

acacia gum, flavor, magnesium stearate, maltodextrin, sugar

Questions?

1-866-651-3660 Monday-Friday 8:00am-5:00pm EST

PRINCIPAL DISPLAY PANEL - 100 Tablet Box

Product #1142

Mint Flavored
Antacid

Active ingredient:
Calcium Carbonate

Stomach Acid Neutralizer

- Great tasting, chewable tablets rich in calcium
- Relieves upset stomach, acid indigestion
  and heartburn

These quality comfort tablets are formulated and packaged for use in the
workplace and meet ANSI Z308.1-2015 standards. They are sealed in
tamper-evident packets for safety and convenience.

100 Tablets • 2 Tablets Per Packet

PRINCIPAL DISPLAY PANEL - 250 Tablet Box

Product #1144

Mint Flavored
Antacid

Active ingredient:
Calcium Carbonate

Stomach Acid Neutralizer

- Great tasting, chewable tablets rich in calcium
- Relieves upset stomach, acid indigestion
  and heartburn

These quality comfort tablets are formulated and packaged for use in the
workplace and meet ANSI Z308.1-2015 standards. They are sealed in
tamper-evident packets for safety and convenience.

250 Tablets • 2 Tablets Per Packet